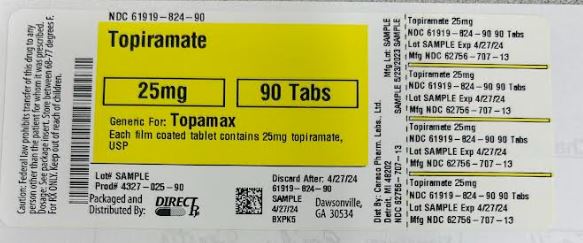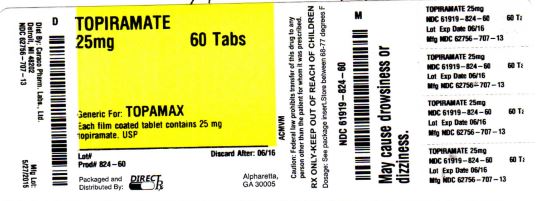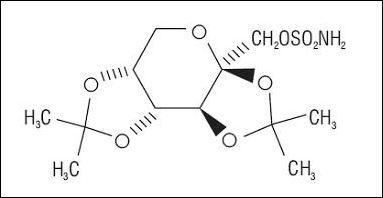 DRUG LABEL: TOPIRAMATE
NDC: 61919-824 | Form: TABLET, FILM COATED
Manufacturer: DIRECT RX
Category: prescription | Type: HUMAN PRESCRIPTION DRUG LABEL
Date: 20230523

ACTIVE INGREDIENTS: TOPIRAMATE 25 mg/1 1
INACTIVE INGREDIENTS: ANHYDROUS LACTOSE; CELLULOSE, MICROCRYSTALLINE; STARCH, CORN; SODIUM STARCH GLYCOLATE TYPE A POTATO; MAGNESIUM STEARATE; POLYVINYL ALCOHOL; TITANIUM DIOXIDE; POLYETHYLENE GLYCOL, UNSPECIFIED; TALC

TOPIRAMATE

DESCRIPTION SECTION

Topiramate is a sulfamate-substituted monosaccharide. Topiramate tablets are available as 25 mg, 50 mg, 100 mg, and 200 mg circular tablets for oral administration.

Topiramate is a white crystalline powder with a bitter taste. Topiramate USP is most soluble in alkaline solutions containing sodium hydroxide or sodium phosphate and having a pH of 9 to 10. It is freely soluble in acetone, chloroform, dimethylsulfoxide, and ethanol. The solubility in water is 9.8 mg/mL. Its saturated solution has a pH of 6.3. Topiramate has the molecular formula C12H21NO8S and a molecular weight of 339.37. Topiramate is designated chemically as 2,3:4,5-Di-O-isopropylidene-β-D-fructopyranose sulfamate and has the following structural formula:

Topiramate tablets contain the following inactive ingredients: anhydrous lactose, microcrystalline cellulose, pregelatinized starch, sodium starch glycolate, magnesium stearate, purified water, polyvinyl alcohol, titanium dioxide, polyethylene glycol and talc.

In addition, individual tablets contain:

50 mg tablets: iron oxide yellow

100 mg tablets: iron oxide yellow, and D&C Yellow # 10 Aluminum Lake

200 mg tablets: iron oxide red, lecithin (soya), and iron oxide black

CLINICAL PHARMACOLOGY

Mechanism of Action:

The precise mechanisms by which topiramate exerts its anticonvulsant effects are unknown; however, preclinical studies have revealed four properties that may contribute to topiramate's efficacy for epilepsy. Electrophysiological and biochemical evidence suggests that topiramate, at pharmacologically relevant concentrations, blocks voltage-dependent sodium channels, augments the activity of the neurotransmitter gamma-aminobutyrate at some subtypes of the GABA-A receptor, antagonizes the AMPA/kainate subtype of the glutamate receptor, and inhibits the carbonic anhydrase enzyme, particularly isozymes II and IV.

Pharmacodynamics:

Topiramate has anticonvulsant activity in rat and mouse maximal electroshock seizure (MES) tests. Topiramate is only weakly effective in blocking clonic seizures induced by the GABAA receptor antagonist, pentylenetetrazole. Topiramate is also effective in rodent models of epilepsy, which include tonic and absence-like seizures in the spontaneous epileptic rat (SER) and tonic and clonic seizures induced in rats by kindling of the amygdala or by global ischemia.

Pharmacokinetics:

The sprinkle formulation is bioequivalent to the immediate release tablet formulation and, therefore, may be substituted as a therapeutic equivalent.

Absorption of topiramate is rapid, with peak plasma concentrations occurring at approximately 2 hours following a 400 mg oral dose. The relative bioavailability of topiramate from the tablet formulation is about 80% compared to a solution. The bioavailability of topiramate is not affected by food.

The pharmacokinetics of topiramate are linear with dose proportional increases in plasma concentration over the dose range studied (200 to 800 mg/day). The mean plasma elimination half-life is 21 hours after single or multiple doses. Steady state is thus reached in about 4 days in patients with normal renal function. Topiramate is 15 to 41% bound to human plasma proteins over the blood concentration range of 0.5 to 250 mcg/mL. The fraction bound decreased as blood concentration increased.

Carbamazepine and phenytoin do not alter the binding of topiramate. Sodium valproate, at 500 mcg/mL (a concentration 5 to 10 times higher than considered therapeutic for valproate) decreased the protein binding of topiramate from 23% to 13%. Topiramate does not influence the binding of sodium valproate.

Metabolism and Excretion:

Topiramate is not extensively metabolized and is primarily eliminated unchanged in the urine (approximately 70% of an administered dose). Six metabolites have been identified in humans, none of which constitutes more than 5% of an administered dose. The metabolites are formed via hydroxylation, hydrolysis, and glucuronidation. There is evidence of renal tubular reabsorption of topiramate. In rats, given probenecid to inhibit tubular reabsorption, along with topiramate, a significant increase in renal clearance of topiramate was observed. This interaction has not been evaluated in humans. Overall, oral plasma clearance (CL/F) is approximately 20 to 30 mL/min in humans following oral administration.

Pharmacokinetic Interactions

(see also Drug Interactions):

Antiepileptic Drugs

Potential interactions between topiramate and standard AEDs were assessed in controlled clinical pharmacokinetic studies in patients with epilepsy. The effect of these interactions on mean plasma AUCs are summarized under PRECAUTIONS (Table 4).

Special Populations:

Renal Impairment:

The clearance of topiramate was reduced by 42% in moderately renally impaired (creatinine clearance 30 to 69 mL/min/1.73m2) and by 54% in severely renally impaired subjects (creatinine clearance <30 mL/min/1.73m2) compared to normal renal function subjects (creatinine clearance >70 mL/min/1.73m2). Since topiramate is presumed to undergo significant tubular reabsorption, it is uncertain whether this experience can be generalized to all situations of renal impairment. It is conceivable that some forms of renal disease could differentially affect glomerular filtration rate and tubular reabsorption resulting in a clearance of topiramate not predicted by creatinine clearance. In general, however, use of one-half the usual starting and maintenance dose is recommended in patients with moderate or severe renal impairment (see PRECAUTIONS: Adjustment of Dose in Renal Failure and DOSAGE AND ADMINISTRATION).

Hemodialysis:

Topiramate is cleared by hemodialysis. Using a high efficiency, counterflow, single pass-dialysate hemodialysis procedure, topiramate dialysis clearance was 120 mL/min with blood flow through the dialyzer at 400 mL/min. This high clearance (compared to 20 to 30 mL/min total oral clearance in healthy adults) will remove a clinically significant amount of topiramate from the patient over the hemodialysis treatment period. Therefore, a supplemental dose may be required (see DOSAGE AND ADMINISTRATION).

Hepatic Impairment:

In hepatically impaired subjects, the clearance of topiramate may be decreased; the mechanism underlying the decrease is not well understood.

Age, Gender, and Race:

The pharmacokinetics of topiramate in elderly subjects (65 to 85 years of age, N=16) were evaluated in a controlled clinical study. The elderly subject population had reduced renal function [creatinine clearance (-20%)] compared to young adults. Following a single oral 100 mg dose, maximum plasma concentration for elderly and young adults was achieved at approximately 1 to 2 hours. Reflecting the primary renal elimination of topiramate, topiramate plasma and renal clearance were reduced 21% and 19%, respectively, in elderly subjects, compared to young adults. Similarly, topiramate half-life was longer (13%) in the elderly. Reduced topiramate clearance resulted in slightly higher maximum plasma concentration (23%) and AUC (25%) in elderly subjects than observed in young adults. Topiramate clearance is decreased in the elderly only to the extent that renal function is reduced. As recommended for all patients, dosage adjustment may be indicated in the elderly patient when impaired renal function (creatinine clearance rate ≤70 mL/min/1.73 m2) is evident. It may be useful to monitor renal function in the elderly patient (see Special Populations: Renal Impairment, PRECAUTIONS: Adjustment of Dose in Renal Failure and DOSAGE AND ADMINISTRATION).

Clearance of topiramate in adults was not affected by gender or race.

Pediatric Pharmacokinetics:

Pharmacokinetics of topiramate were evaluated in patients ages 4 to 17 years receiving one or two other antiepileptic drugs. Pharmacokinetic profiles were obtained after one week at doses of 1, 3, and 9 mg/kg/day. Clearance was independent of dose.

Pediatric patients have a 50% higher clearance and consequently shorter elimination half-life than adults. Consequently, the plasma concentration for the same mg/kg dose may be lower in pediatric patients compared to adults. As in adults, hepatic enzyme-inducing antiepileptic drugs decrease the steady state plasma concentrations of topiramate.

CLINICAL STUDIES

The studies described in the following sections were conducted using topiramate tablets.

EpilepsyMonotherapy Controlled Trial

The effectiveness of topiramate as initial monotherapy in adults and children 10 years of age and older with partial onset or primary generalized seizures was established in a multicenter, randomized, double-blind, parallel-group trial.

The trial was conducted in 487 patients diagnosed with epilepsy (6 to 83 years of age) who had 1 or 2 well-documented seizures during the 3-month retrospective baseline phase who then entered the study and received topiramate 25 mg/day for 7 days in an open-label fashion. Forty-nine percent of subjects had no prior AED treatment and 17% had a diagnosis of epilepsy for greater than 24 months. Any AED therapy used for temporary or emergency purposes was discontinued prior to randomization. In the double-blind phase, 470 patients were randomized to titrate up to 50 mg/day or 400 mg/day. If the target dose could not be achieved, patients were maintained on the maximum tolerated dose. Fifty eight percent of patients achieved the maximal dose of 400 mg/day for ≥ 2 weeks, and patients who did not tolerate 150 mg/day were discontinued. The primary efficacy assessment was a between group comparison of time to first seizure during the double-blind phase. Comparison of the Kaplan-Meier survival curves of time to first seizure favored the topiramate 400 mg/day group over the topiramate 50 mg/day group (p=0.0002, log rank test; Figure 1). The treatment effects with respect to time to first seizure were consistent across various patient subgroups defined by age, sex, geographic region, baseline body weight, baseline seizure type, time since diagnosis, and baseline AED use.

Figure 1: Kaplan-Meier Estimates of Cumulative Rates for Time to First Seizure

Adjunctive Therapy Controlled Trials in Patients With Partial Onset Seizures

The effectiveness of topiramate as an adjunctive treatment for adults with partial onset seizures was established in six multicenter, randomized, double-blind, placebo-controlled trials, two comparing several dosages of topiramate and placebo and four comparing a single dosage with placebo, in patients with a history of partial onset seizures, with or without secondarily generalized seizures.

Patients in these studies were permitted a maximum of two antiepileptic drugs (AEDs) in addition to topiramate tablets or placebo. In each study, patients were stabilized on optimum dosages of their concomitant AEDs during baseline phase lasting between 4 and 12 weeks. Patients who experienced a prespecified minimum number of partial onset seizures, with or without secondary generalization, during the baseline phase (12 seizures for 12-week baseline, 8 for 8-week baseline, or 3 for 4-week baseline) were randomly assigned to placebo or a specified dose of topiramate tablets in addition to their other AEDs.

Following randomization, patients began the double-blind phase of treatment. In five of the six studies, patients received active drug beginning at 100 mg per day; the dose was then increased by 100 mg or 200 mg/day increments weekly or every other week until the assigned dose was reached, unless intolerance prevented increases. In the sixth study (119), the 25 or 50 mg/day initial doses of topiramate were followed by respective weekly increments of 25 or 50 mg/day until the target dose of 200 mg/day was reached. After titration, patients entered a 4, 8, or 12-week stabilization period. The numbers of patients randomized to each dose, and the actual mean and median doses in the stabilization period are shown in Table 1.

Adjunctive Therapy Controlled Trial in Pediatric Patients Ages 2 to 16 Years With Partial Onset Seizures

The effectiveness of topiramate as an adjunctive treatment for pediatric patients ages 2 to 16 years with partial onset seizures was established in a multicenter, randomized, double-blind, placebo-controlled trial, comparing topiramate and placebo in patients with a history of partial onset seizures, with or without secondarily generalized seizures.

Patients in this study were permitted a maximum of two antiepileptic drugs (AEDs) in addition to topiramate tablets or placebo. In this study, patients were stabilized on optimum dosages of their concomitant AEDs during an 8-week baseline phase. Patients who experienced at least six partial onset seizures, with or without secondarily generalized seizures, during the baseline phase were randomly assigned to placebo or topiramate tablets in addition to their other AEDs.

Following randomization, patients began the double-blind phase of treatment. Patients received active drug beginning at 25 or 50 mg per day; the dose was then increased by 25 mg to 150 mg/day increments every other week until the assigned dosage of 125, 175, 225, or 400 mg/day based on patients' weight to approximate a dosage of 6 mg/kg per day was reached, unless intolerance prevented increases. After titration, patients entered an 8-week stabilization period.

Adjunctive Therapy Controlled Trial in Patients With Primary Generalized Tonic-Clonic Seizures

The effectiveness of topiramate as an adjunctive treatment for primary generalized tonic-clonic seizures in patients 2 years old and older was established in a multicenter, randomized, double-blind, placebo-controlled trial, comparing a single dosage of topiramate and placebo.

Patients in this study were permitted a maximum of two antiepileptic drugs (AEDs) in addition to topiramate or placebo. Patients were stabilized on optimum dosages of their concomitant AEDs during an 8-week baseline phase. Patients who experienced at least three primary generalized tonic-clonic seizures during the baseline phase were randomly assigned to placebo or topiramate in addition to their other AEDs.

Following randomization, patients began the double-blind phase of treatment. Patients received active drug beginning at 50 mg per day for four weeks; the dose was then increased by 50 mg to 150 mg/day increments every other week until the assigned dose of 175, 225, or 400 mg/day based on patients' body weight to approximate a dosage of 6 mg/kg per day was reached, unless intolerance prevented increases. After titration, patients entered a 12-week stabilization period.

Adjunctive Therapy Controlled Trial in Patients With Lennox-Gastaut Syndrome

The effectiveness of topiramate as an adjunctive treatment for seizures associated with Lennox-Gastaut syndrome was established in a multicenter, randomized, double-blind, placebo-controlled trial comparing a single dosage of topiramate with placebo in patients 2 years of age and older.

Patients in this study were permitted a maximum of two antiepileptic drugs (AEDs) in addition to topiramate or placebo. Patients who were experiencing at least 60 seizures per month before study entry were stabilized on optimum dosages of their concomitant AEDs during a 4-week baseline phase. Following baseline, patients were randomly assigned to placebo or topiramate in addition to their other AEDs. Active drug was titrated beginning at 1 mg/kg per day for a week; the dose was then increased to 3 mg/kg per day for one week then to 6 mg/kg per day. After titration, patients entered an 8-week stabilization period. The primary measures of effectiveness were the percent reduction in drop attacks and a parental global rating of seizure severity.

Table 1: Topiramate Dose Summary During the Stabilization Periods of Each of Six Double-Blind, Placebo-Controlled, Add-On Trials in Adults with Partial Onset Seizuresb
Target Topiramate Dosage (mg/day)
Protocol Stabilization Dose Placeboa 200 400 600 800 1,000

a Placebo dosages are given as the number of tablets. Placebo target dosages were as follows: Protocol Y1, 4 tablets/day; Protocols YD and Y2, 6 tablets/day; Protocol Y3 and 119, 8 tablets/day; Protocol YE, 10 tablets/day.

b Dose-response studies were not conducted for other indications or pediatric partial onset seizures.

YD N 42 42 40 41 -- --
Mean Dose 5.9 200 390 556 -- --
Median Dose 6.0 200 400 600 -- --
YE N 44 -- -- 40 45 40
Mean Dose 9.7 -- -- 544 739 796
Median Dose 10.0 -- -- 600 800 1,000
Y1 N 23 -- 19 -- -- --
Mean Dose 3.8 -- 395 -- -- --
Median Dose 4.0 -- 400 -- -- --
Y2 N 30 -- -- 28 -- --
Mean Dose 5.7 -- -- 522 -- --
Median Dose 6.0 -- -- 600 -- --
Y3 N 28 -- -- -- 25 --
Mean Dose 7.9 -- -- -- 568 --
Median Dose 8.0 -- -- -- 600 --
119 N 90 157 -- -- -- --
Mean Dose 8 200 -- -- -- --
Median Dose 8 200 -- -- -- --

In all add-on trials, the reduction in seizure rate from baseline during the entire double-blind phase was measured. The median percent reductions in seizure rates and the responder rates (fraction of patients with at least a 50% reduction) by treatment group for each study are shown below in Table 2. As described above, a global improvement in seizure severity was also assessed in the Lennox-Gastaut trial.

Table 2: Efficacy Results in Double-Blind, Placebo-Controlled, Add-On Epilepsy Trials
Target Topiramate Dosage (mg/day)
Protocol Efficacy Results Placebo 200 400 600 800 1,000 ≈6
mg/kg/day*

Comparisons with placebo: a p=0.080; b p<0.010; c p<0.001; d p<0.050; e p=0.065; f p<0.005;g p=0.071;

h Median % reduction and % responders are reported for PGTC Seizures;

i Median % reduction and % responders for drop attacks, i.e., tonic or atonic seizures;

j Percent of subjects who were minimally, much, or very much improved from baseline

* For Protocols YP and YTC, protocol-specified target dosages (<9.3 mg/kg/day) were assigned based on subject's weight to approximate a dosage of 6 mg/kg per day; these dosages corresponded to mg/day dosages of 125, 175, 225, and 400 mg/day.

Partial Onset Seizures
Studies in Adults
YD N 45 45 45 46 -- -- --
Median % Reduction 11.6 27.2a 47.5b 44.7c -- -- --
% Responders 18 24 44d 46d -- -- --
YE N 47 -- -- 48 48 47 --
Median % Reduction 1.7 -- -- 40.8c 41.0c 36.0c --
% Responders 9 -- -- 40c 41c 36d --
Y1 N 24 -- 23 -- -- -- --
Median % Reduction 1.1 -- 40.7e -- -- -- --
% Responders 8 -- 35d -- -- -- --
Y2 N 30 -- -- 30 -- -- --
Median % Reduction -12.2 -- -- 46.4f -- -- --
% Responders 10 -- -- 47c -- -- --
Y3 N 28 -- -- -- 28 -- --
Median % Reduction -20.6 -- -- -- 24.3c -- --
% Responders 0 -- -- -- 43c -- --
119 N 91 168 -- -- -- -- --
Median % Reduction 20.0 44.2c -- -- -- -- --
% Responders 24 45c -- -- -- -- --
Studies in Pediatric Patients
YP N 45 -- -- -- -- -- 41
Median % Reduction 10.5 -- -- -- -- -- 33.1d
% Responders 20 -- -- -- -- -- 39
Primary Generalized Tonic-Clonich
YTC N 40 -- -- -- -- -- 39
Median % Reduction 9.0 -- -- -- -- -- 56.7d
% Responders 20 -- -- -- -- -- 56c
Lennox-Gastaut Syndromei
YL N 49 -- -- -- -- -- 46
Median % Reduction -5.1 -- -- -- -- -- 14.8d
% Responders 14 -- -- -- -- -- 28g
Improvement in Seizure Severityj 28 -- -- -- -- -- 52d

Subset analyses of the antiepileptic efficacy of topiramate tablets in these studies showed no differences as a function of gender, race, age, baseline seizure rate, or concomitant AED.

INDICATIONS & USAGE SECTION

INDICATIONS AND USAGEMonotherapy Epilepsy

Topiramate tablets are indicated as initial monotherapy in patients 10 years of age and older with partial onset or primary generalized tonic-clonic seizures.

Effectiveness was demonstrated in a controlled trial in patients with epilepsy who had no more than 2 seizures in the 3 months prior to enrollment. Safety and effectiveness in patients who were converted to monotherapy from a previous regimen of other anticonvulsant drugs have not been established in controlled trials.

Adjunctive Therapy Epilepsy

Topiramate tablets are indicated as adjunctive therapy for adults and pediatric patients ages 2 to 16 years with partial onset seizures, or primary generalized tonic-clonic seizures, and in patients 2 years of age and older with seizures associated with Lennox-Gastaut syndrome.

CONTRAINDICATIONS SECTION

Topiramate tablets are contraindicated in patients with a history of hypersensitivity to any component of this product.

WARNINGS SECTION

Acute Myopia and Secondary Angle Closure Glaucoma

A syndrome consisting of acute myopia associated with secondary angle closure glaucoma has been reported in patients receiving topiramate. Symptoms include acute onset of decreased visual acuity and/or ocular pain. Ophthalmologic findings can include myopia, anterior chamber shallowing, ocular hyperemia (redness) and increased intraocular pressure. Mydriasis may or may not be present. This syndrome may be associated with supraciliary effusion resulting in anterior displacement of the lens and iris, with secondary angle closure glaucoma. Symptoms typically occur within 1 month of initiating topiramate therapy. In contrast to primary narrow angle glaucoma, which is rare under 40 years of age, secondary angle closure glaucoma associated with topiramate has been reported in pediatric patients as well as adults. The primary treatment to reverse symptoms is discontinuation of topiramate as rapidly as possible, according to the judgment of the treating physician. Other measures, in conjunction with discontinuation of topiramate, may be helpful.

Elevated intraocular pressure of any etiology, if left untreated, can lead to serious sequelae including permanent vision loss.

Oligohidrosis and Hyperthermia

Oligohidrosis (decreased sweating), infrequently resulting in hospitalization, has been reported in association with topiramate use. Decreased sweating and an elevation in body temperature above normal characterized these cases. Some of the cases were reported after exposure to elevated environmental temperatures.

The majority of the reports have been in children. Patients, especially pediatric patients, treated with topiramate should be monitored closely for evidence of decreased sweating and increased body temperature, especially in hot weather. Caution should be used when topiramate is prescribed with other drugs that predispose patients to heat-related disorders; these drugs include, but are not limited to, other carbonic anhydrase inhibitors and drugs with anticholinergic activity.

Suicidal Behavior and Ideation

Antiepileptic drugs (AEDs), including topiramate, increase the risk of suicidal thoughts or behavior in patients taking these drugs for any indication. Patients treated with any AED for any indication should be monitored for the emergence or worsening of depression, suicidal thoughts or behavior, and/or any unusual changes in mood or behavior.

Pooled analyses of 199 placebo-controlled clinical trials (mono- and adjunctive therapy) of 11 different AEDs showed that patients randomized to one of the AEDs had approximately twice the risk (adjusted Relative Risk 1.8, 95% CI:1.2, 2.7) of suicidal thinking or behavior compared to patients randomized to placebo. In these trials, which had a median treatment duration of 12 weeks, the estimated incidence rate of suicidal behavior or ideation among 27,863 AED-treated patients was 0.43%, compared to 0.24% among 16,029 placebo-treated patients, representing an increase of approximately one case of suicidal thinking or behavior for every 530 patients treated. There were four suicides in drug-treated patients in the trials and none in placebo-treated patients, but the number is too small to allow any conclusion about drug effect on suicide.

The increased risk of suicidal thoughts or behavior with AEDs was observed as early as one week after starting drug treatment with AEDs and persisted for the duration of treatment assessed. Because most trials included in the analysis did not extend beyond 24 weeks, the risk of suicidal thoughts or behavior beyond 24 weeks could not be assessed.

The risk of suicidal thoughts or behavior was generally consistent among drugs in the data analyzed. The finding of increased risk with AEDs of varying mechanisms of action and across a range of indications suggests that the risk applies to all AEDs used for any indication. The risk did not vary substantially by age (5 to 100 years) in the clinical trials analyzed.

Table 3 shows absolute and relative risk by indication for all evaluated AEDs.

Table 3 Risk by Indication for Antiepileptic Drugs in the Pooled Analysis
Indication | Placebo Patients with Events Per 1000 Patients | Drug Patients with Events Per 1000 Patients | Relative Risk: Incidence of Events in Drug Patients/Incidence in Placebo Patients | Risk Difference: Additional Drug Patients with Events Per 1000 Patients
Epilepsy | 1.0 | 3.4 | 3.5 | 2.4
Psychiatric | 5.7 | 8.5 | 1.5 | 2.9
Other | 1.0 | 1.8 | 1.9 | 0.9
Total | 2.4 | 4.3 | 1.8 | 1.9

The relative risk for suicidal thoughts or behavior was higher in clinical trials for epilepsy than in clinical trials for psychiatric or other conditions, but the absolute risk differences were similar for the epilepsy and psychiatric indications.

Anyone considering prescribing topiramate or any other AED must balance the risk of suicidal thoughts or behavior with the risk of untreated illness. Epilepsy and many other illnesses for which AEDs are prescribed are themselves associated with morbidity and mortality and an increased risk of suicidal thoughts and behavior. Should suicidal thoughts and behavior emerge during treatment, the prescriber needs to consider whether the emergence of these symptoms in any given patient may be related to the illness being treated.

Patients, their caregivers, and families should be informed that AEDs increase the risk of suicidal thoughts and behavior and should be advised of the need to be alert for the emergence or worsening of the signs and symptoms of depression, any unusual changes in mood or behavior or the emergence of suicidal thoughts, behavior or thoughts about self-harm. Behaviors of concern should be reported immediately to healthcare providers.

Metabolic Acidosis

Hyperchloremic, non-anion gap, metabolic acidosis (i.e., decreased serum bicarbonate below the normal reference range in the absence of chronic respiratory alkalosis) is associated with topiramate treatment. This metabolic acidosis is caused by renal bicarbonate loss due to the inhibitory effect of topiramate on carbonic anhydrase. Such electrolyte imbalance has been observed with the use of topiramate in placebo-controlled clinical trials and in the post-marketing period. Generally, topiramate-induced metabolic acidosis occurs early in treatment although cases can occur at any time during treatment. Bicarbonate decrements are usually mild-moderate (average decrease of 4 mEq/L at daily doses of 400 mg in adults and at approximately 6 mg/kg/day in pediatric patients); rarely, patients can experience severe decrements to values below 10 mEq/L. Conditions or therapies that predispose to acidosis (such as renal disease, severe respiratory disorders, status epilepticus, diarrhea, surgery, ketogenic diet, or drugs) may be additive to the bicarbonate lowering effects of topiramate.

In adults, the incidence of persistent treatment-emergent decreases in serum bicarbonate (levels of <20 mEq/L at two consecutive visits or at the final visit) in controlled clinical trials for adjunctive treatment of epilepsy was 32% for 400 mg/day, and 1% for placebo. Metabolic acidosis has been observed at doses as low as 50 mg/day. The incidence of persistent treatment-emergent decreases in serum bicarbonate in adults in the epilepsy controlled clinical trial for monotherapy was 15% for 50 mg/day and 25% for 400 mg/day. The incidence of a markedly abnormally low serum bicarbonate (i.e., absolute value <17 mEq/L and >5 mEq/L decrease from pretreatment) in the adjunctive therapy trials was 3% for 400 mg/day, and 0% for placebo and in the monotherapy trial was 1% for 50 mg/day and 7% for 400 mg/day. Serum bicarbonate levels have not been systematically evaluated at daily doses greater than 400 mg/day.

In pediatric patients (<16 years of age), the incidence of persistent treatment-emergent decreases in serum bicarbonate in placebo-controlled trials for adjunctive treatment of Lennox-Gastaut syndrome or refractory partial onset seizures was 67% for topiramate (at approximately 6 mg/kg/day), and 10% for placebo. The incidence of a markedly abnormally low serum bicarbonate (i.e., absolute value <17 mEq/L and >5 mEq/L decrease from pretreatment) in these trials was 11% for topiramate and 0% for placebo. Cases of moderately severe metabolic acidosis have been reported in patients as young as 5 months old, especially at daily doses above 5 mg/kg/day.

In pediatric patients (10 years up to 16 years of age), the incidence of persistent treatment-emergent decreases in serum bicarbonate in the epilepsy controlled clinical trial for monotherapy was 7% for 50 mg/day and 20% for 400 mg/day. The incidence of a markedly abnormally low serum bicarbonate (i.e., absolute value <17 mEq/L and >5 mEq/L decrease from pretreatment) in this trial was 4% for 50 mg/day and 4% for 400 mg/day.

Some manifestations of acute or chronic metabolic acidosis may include hyperventilation, nonspecific symptoms such as fatigue and anorexia, or more severe sequelae including cardiac arrhythmias or stupor. Chronic, untreated metabolic acidosis may increase the risk for nephrolithiasis or nephrocalcinosis, and may also result in osteomalacia (referred to as rickets in pediatric patients) and/or osteoporosis with an increased risk for fractures. Chronic metabolic acidosis in pediatric patients may also reduce growth rates. A reduction in growth rate may eventually decrease the maximal height achieved. The effect of topiramate on growth and bone-related sequelae has not been systematically investigated.

Measurement of baseline and periodic serum bicarbonate during topiramate treatment is recommended. If metabolic acidosis develops and persists, consideration should be given to reducing the dose or discontinuing topiramate (using dose tapering). If the decision is made to continue patients on topiramate in the face of persistent acidosis, alkali treatment should be considered.

Cognitive/Neuropsychiatric Adverse EventsAdults

Adverse events most often associated with the use of topiramate were related to the central nervous system and were observed in the epilepsy population. In adults, the most frequent of these can be classified into three general categories: 1) Cognitive-related dysfunction (e.g. confusion, psychomotor slowing, difficulty with concentration/attention, difficulty with memory, speech or language problems, particularly word-finding difficulties); 2) Psychiatric/behavioral disturbances (e.g. depression or mood problems); and 3) Somnolence or fatigue.

Cognitive-Related Dysfunction

The majority of cognitive-related adverse events were mild to moderate in severity, and they frequently occurred in isolation. Rapid titration rate and higher initial dose were associated with higher incidences of these events. Many of these events contributed to withdrawal from treatment [see ADVERSE REACTIONS, Table 5 and Table 7].

In the original add-on epilepsy controlled trials (using rapid titration such as 100 to 200 mg/day weekly increments), the proportion of patients who experienced one or more cognitive-related adverse events was 42% for 200 mg/day, 41% for 400 mg/day, 52% for 600 mg/day, 56% for 800 and 1000 mg/day, and 14% for placebo. These dose-related adverse reactions began with a similar frequency in the titration or in the maintenance phase, although in some patients the events began during titration and persisted into the maintenance phase. Some patients who experienced one or more cognitive-related adverse events in the titration phase had a dose-related recurrence of these events in the maintenance phase.

In the monotherapy epilepsy controlled trial, the proportion of patients who experienced one or more cognitive-related adverse events was 19% for topiramate 50 mg/day and 26% for 400 mg/day.

Psychiatric/Behavioral Disturbances

Psychiatric/behavioral disturbances (depression or mood problems) were dose-related for the epilepsy population.

Somnolence/Fatigue

Somnolence and fatigue were the adverse events most frequently reported during clinical trials of topiramate for adjunctive epilepsy. For the adjunctive epilepsy population, the incidence of somnolence did not differ substantially between 200 mg/day and 1000 mg/day, but the incidence of fatigue was dose-related and increased at dosages above 400 mg/day. For the monotherapy epilepsy population in the 50 mg/day and 400 mg/day groups, the incidence of somnolence was dose-related (9% for the 50 mg/day group and 15% for the 400 mg/day group) and the incidence of fatigue was comparable in both treatment groups (14% each).

Additional nonspecific CNS events commonly observed with topiramate in the add-on epilepsy population include dizziness or ataxia.

Pediatric Patients

In double-blind adjunctive therapy and monotherapy epilepsy clinical studies, the incidences of cognitive/neuropsychiatric adverse events in pediatric patients were generally lower than observed in adults. These events included psychomotor slowing, difficulty with concentration/attention, speech disorders/related speech problems and language problems. The most frequently reported neuropsychiatric events in pediatric patients during adjunctive therapy double-blind studies were somnolence and fatigue. The most frequently reported neuropsychiatric events in pediatric patients in the 50 mg/day and 400 mg/day groups during the monotherapy double-blind study were headache, dizziness, anorexia, and somnolence.

No patients discontinued treatment due to any adverse events in the adjunctive epilepsy double-blind trials. In the monotherapy epilepsy double-blind trial, 1 pediatric patient (2%) in the 50 mg/day group and 7 pediatric patients (12%) in the 400 mg/day group discontinued treatment due to any adverse events. The most common adverse event associated with discontinuation of therapy was difficulty with concentration/attention; all occurred in the 400 mg/day group.

Withdrawal of AEDs

Antiepileptic drugs, including topiramate, should be withdrawn gradually to minimize the potential of increased seizure frequency.

Sudden Unexplained Death in Epilepsy (SUDEP)

During the course of premarketing development of topiramate tablets, 10 sudden and unexplained deaths were recorded among a cohort of treated patients (2,796 subject years of exposure). This represents an incidence of 0.0035 deaths per patient year. Although this rate exceeds that expected in a healthy population matched for age and sex, it is within the range of estimates for the incidence of sudden unexplained deaths in patients with epilepsy not receiving topiramate (ranging from 0.0005 for the general population of patients with epilepsy, to 0.003 for a clinical trial population similar to that in the topiramate program, to 0.005 for patients with refractory epilepsy).

PRECAUTIONS SECTION

Hyperammonemia and Encephalopathy Associated with Concomitant Valproic Acid Use

Concomitant administration of topiramate and valproic acid has been associated with hyperammonemia with or without encephalopathy in patients who have tolerated either drug alone. Clinical symptoms of hyperammonemic encephalopathy often include acute alterations in level of consciousness and/or cognitive function with lethargy or vomiting. In most cases, symptoms and signs abated with discontinuation of either drug. This adverse event is not due to a pharmacokinetic interaction.

It is not known if topiramate monotherapy is associated with hyperammonemia.

Patients with inborn errors of metabolism or reduced hepatic mitochondrial activity may be at an increased risk for hyperammonemia with or without encephalopathy. Although not studied, an interaction of topiramate and valproic acid may exacerbate existing defects or unmask deficiencies in susceptible persons.

In patients who develop unexplained lethargy, vomiting, or changes in mental status, hyperammonemic encephalopathy should be considered and an ammonia level should be measured.

Kidney Stones

A total of 32/2,086 (1.5%) of adults exposed to topiramate during its adjunctive epilepsy therapy development reported the occurrence of kidney stones, an incidence about 2 to 4 times greater than expected in a similar, untreated population. In the double-blind monotherapy epilepsy study, a total of 4/319 (1.3%) of adults exposed to topiramate reported the occurrence of kidney stones. As in the general population, the incidence of stone formation among topiramate treated patients was higher in men. Kidney stones have also been reported in pediatric patients.

An explanation for the association of topiramate and kidney stones may lie in the fact that topiramate is a carbonic anhydrase inhibitor. Carbonic anhydrase inhibitors, e.g., acetazolamide or dichlorphenamide, promote stone formation by reducing urinary citrate excretion and by increasing urinary pH. The concomitant use of topiramate with other carbonic anhydrase inhibitors or potentially in patients on a ketogenic diet may create a physiological environment that increases the risk of kidney stone formation, and should therefore be avoided.

Increased fluid intake increases the urinary output, lowering the concentration of substances involved in stone formation. Hydration is recommended to reduce new stone formation.

Paresthesia

Paresthesia (usually tingling of the extremities), an effect associated with the use of other carbonic anhydrase inhibitors, appears to be a common effect of topiramate. Paresthesia was more frequently reported in the monotherapy epilepsy trials versus the adjunctive therapy epilepsy trials. In the majority of instances, paresthesia did not lead to treatment discontinuation.

Adjustment of Dose in Renal Failure

The major route of elimination of unchanged topiramate and its metabolites is via the kidney. Dosage adjustment may be required in patients with reduced renal function (see DOSAGE AND ADMINISTRATION).

Decreased Hepatic Function

In hepatically impaired patients, topiramate should be administered with caution as the clearance of topiramate may be decreased.

Information for Patients

Patients and their caregivers should be informed of the availability of a Medication Guide, and they should be instructed to read the Medication Guide prior to taking topiramate tablets. Patients should be instructed to take topiramate tablets only as prescribed.

Patients taking topiramate should be told to seek immediate medical attention if they experience blurred vision or periorbital pain.

Patients, especially pediatric patients, treated with topiramate should be monitored closely for evidence of decreased sweating and increased body temperature, especially in hot weather.

Patients, their caregivers, and families should be counseled that AEDs, including topiramate, may increase the risk of suicidal thoughts and behavior and should be advised of the need to be alert for the emergence or worsening of symptoms of depression, any unusual changes in mood or behavior or the emergence of suicidal thoughts, behavior or thoughts about self-harm. Behaviors of concern should be reported immediately to healthcare providers.

Patients, particularly those with predisposing factors, should be instructed to maintain an adequate fluid intake in order to minimize the risk of renal stone formation (see PRECAUTIONS: Kidney Stones, for support regarding hydration as a preventative measure).

Patients should be warned about the potential for somnolence, dizziness, confusion, and difficulty concentrating, and advised not to drive or operate machinery until they have gained sufficient experience on topiramate to gauge whether it adversely affects their mental performance and/or motor performance.

Additional food intake may be considered if the patient is losing weight while on this medication.

Patients should be encouraged to enroll in the North American Antiepileptic Drug (NAAED) Pregnancy Registry if they become pregnant. This registry is collecting information about the safety of antiepileptic drugs during pregnancy. To enroll, patients can call the toll free number, 1-888-233-2334 (see PRECAUTIONS: Pregnancy: Pregnancy Category C).

Laboratory Tests:

Measurement of baseline and periodic serum bicarbonate during topiramate treatment is recommended (see WARNINGS).

Drug Interactions:

In vitro studies indicate that topiramate does not inhibit enzyme activity for CYP1A2, CYP2A6, CYP2B6, CYP2C9, CYP2C19, CYP2D6, CYP2E1 and CYP3A4/5 isozymes.

Antiepileptic Drugs

Potential interactions between topiramate and standard AEDs were assessed in controlled clinical pharmacokinetic studies in patients with epilepsy. The effects of these interactions on mean plasma AUCs are summarized in Table 4.

In Table 4, the second column (AED concentration) describes what happens to the concentration of the AED listed in the first column when topiramate is added.

The third column (topiramate concentration) describes how the coadministration of a drug listed in the first column modifies the concentration of topiramate in experimental settings when topiramate was given alone.

Table 4: Summary of AED Interactions with Topiramate
AED Co-administered | AED Concentration | Topiramate Concentration
Phenytoin | NC or 25% increasea | 48% decrease
Carbamazepine (CBZ) | NC | 40% decrease
CBZ epoxideb | NC | NE
Valproic acid | 11% decrease | 14% decrease
Phenobarbital | NC | NE
Primidone | NC | NE
Lamotrigine | NC at TPM doses up to 400 mg/day | 15% increase
a = Plasma concentration increased 25% in some patients, generally those on a b.i.d. dosing regimen of phenytoin.
b = Is not administered but is an active metabolite of carbamazepine.
NC = Less than 10% change in plasma concentration.
AED = Antiepileptic drug.
NE = Not Evaluated.
TPM = Topiramate

In addition to the pharmacokinetic interaction described in the above table, concomitant administration of valproic acid and topiramate has been associated with hyperammonemia with and without encephalopathy (see PRECAUTIONS, Hyperammonemia and Encephalopathy Associated with Concomitant Valproic Acid Use).

Other Drug InteractionsDigoxin

In a single-dose study, serum digoxin AUC was decreased by 12% with concomitant topiramate administration. The clinical relevance of this observation has not been established.

CNS Depressants

Concomitant administration of topiramate and alcohol or other CNS depressant drugs has not been evaluated in clinical studies. Because of the potential of topiramate to cause CNS depression, as well as other cognitive and/or neuropsychiatric adverse events, topiramate should be used with extreme caution if used in combination with alcohol and other CNS depressants.

Oral Contraceptives

In a pharmacokinetic interaction study in healthy volunteers with a concomitantly administered combination oral contraceptive product containing 1 mg norethindrone (NET) plus 35 mcg ethinyl estradiol (EE), topiramate given in the absence of other medications at doses of 50 to 200 mg/day was not associated with statistically significant changes in mean exposure (AUC) to either component of the oral contraceptive. In another study, exposure to EE was statistically significantly decreased at doses of 200, 400, and 800 mg/day (18%, 21%, and 30%, respectively) when given as adjunctive therapy in patients taking valproic acid. In both studies, topiramate (50 mg/day to 800 mg/day) did not significantly affect exposure to NET. Although there was a dose dependent decrease in EE exposure for doses between 200 to 800 mg/day, there was no significant dose dependent change in EE exposure for doses of 50 to 200 mg/day. The clinical significance of the changes observed is not known. The possibility of decreased contraceptive efficacy and increased breakthrough bleeding should be considered in patients taking combination oral contraceptive products with topiramate. Patients taking estrogen containing contraceptives should be asked to report any change in their bleeding patterns. Contraceptive efficacy can be decreased even in the absence of breakthrough bleeding.

Hydrochlorothiazide (HCTZ)

A drug-drug interaction study conducted in healthy volunteers evaluated the steady-state pharmacokinetics of HCTZ (25 mg q24h) and topiramate (96 mg q12h) when administered alone and concomitantly. The results of this study indicate that topiramate Cmax increased by 27% and AUC increased by 29% when HCTZ was added to topiramate. The clinical significance of this change is unknown. The addition of HCTZ to topiramate therapy may require an adjustment of the topiramate dose. The steady-state pharmacokinetics of HCTZ were not significantly influenced by the concomitant administration of topiramate. Clinical laboratory results indicated decreases in serum potassium after topiramate or HCTZ administration, which were greater when HCTZ and topiramate were administered in combination.

Pioglitazone

A drug-drug interaction study conducted in healthy volunteers evaluated the steady-state pharmacokinetics of topiramate and pioglitazone when administered alone and concomitantly. A 15% decrease in the AUCτ,ss of pioglitazone with no alteration in Cmax,ss was observed. This finding was not statistically significant. In addition, a 13% and 16% decrease in Cmax,ss and AUCτ,ss respectively, of the active hydroxy-metabolite was noted as well as a 60% decrease in Cmax,ss and AUCτ,ss of the active keto-metabolite. The clinical significance of these findings is not known. When topiramate is added to pioglitazone therapy or pioglitazone is added to topiramate therapy, careful attention should be given to the routine monitoring of patients for adequate control of their diabetic disease state.

Lithium

Multiple dosing of topiramate 100 mg every 12 hrs decreased the AUC and cmax of Lithium (300 mg every 8 hrs) by 20% (N=12, 6 M; 6 F).

Haloperidol

The pharmacokinetics of a single dose of haloperidol (5 mg) were not affected following multiple dosing of topiramate (100 mg every 12 hr) in 13 healthy adults (6 M, 7 F).

Amitriptyline

There was a 12% increase in AUC and Cmax for amitriptyline (25 mg per day) in 18 normal subjects (9 male; 9 female) receiving 200 mg/day of topiramate. Some subjects may experience a large increase in amitriptyline concentration in the presence of topiramate and any adjustments in amitriptyline dose should be made according to the patient's clinical response and not on the basis of plasma levels.

Sumatriptan

Multiple dosing of topiramate (100 mg every 12 hrs) in 24 healthy volunteers (14 M, 10 F) did not affect the pharmacokinetics of single dose sumatriptan either orally (100 mg) or subcutaneously (6 mg).

Risperidone

There was a 25% decrease in exposure to risperidone (2 mg single dose) in 12 healthy volunteers (6 M, 6 F) receiving 200 mg/day of topiramate. Therefore, patients receiving risperidone in combination with topiramate should be closely monitored for clinical response.

Propranolol

Multiple dosing of topiramate (200 mg/day) in 34 healthy volunteers (17 M, 17 F) did not affect the pharmacokinetics of propranolol following daily 160 mg doses. Propranolol doses of 160 mg/day in 39 volunteers (27M, 12F) had no effect on the exposure to topiramate at a dose of 200 mg/day of topiramate.

Dihydroergotamine

Multiple dosing of topiramate (200 mg/day) in 24 healthy volunteers (12 M, 12 F) did not affect the pharmacokinetics of a 1 mg subcutaneous dose of dihydroergotamine. Similarly, a 1 mg subcutaneous dose of dihydroergotamine did not affect the pharmacokinetics of a 200 mg/day dose of topiramate in the same study.

Others

Concomitant use of topiramate, a carbonic anhydrase inhibitor, with other carbonic anhydrase inhibitors, e.g., acetazolamide or dichlorphenamide, may create a physiological environment that increases the risk of renal stone formation, and should therefore be avoided.

Drug/Laboratory Tests Interactions

There are no known interactions of topiramate with commonly used laboratory tests.

Carcinogenesis, Mutagenesis, Impairment of Fertility:

An increase in urinary bladder tumors was observed in mice given topiramate (20, 75, and 300 mg/kg) in the diet for 21 months. The elevated bladder tumor incidence, which was statistically significant in males and females receiving 300 mg/kg, was primarily due to the increased occurrence of a smooth muscle tumor considered histomorphologically unique to mice. Plasma exposures in mice receiving 300 mg/kg were approximately 0.5 to 1 times steady-state exposures measured in patients receiving topiramate monotherapy at the recommended human dose (RHD) of 400 mg, and 1.5 to 2 times steady-state topiramate exposures in patients receiving 400 mg of topiramate plus phenytoin. The relevance of this finding to human carcinogenic risk is uncertain. No evidence of carcinogenicity was seen in rats following oral administration of topiramate for 2 years at doses up to 120 mg/kg (approximately 3 times the RHD on a mg/m2 basis).

Topiramate did not demonstrate genotoxic potential when tested in a battery of in vitro and in vivo assays. Topiramate was not mutagenic in the Ames test or the in vitro mouse lymphoma assay; it did not increase unscheduled DNA synthesis in rat hepatocytes in vitro; and it did not increase chromosomal aberrations in human lymphocytes in vitro or in rat bone marrow in vivo.

No adverse effects on male or female fertility were observed in rats at doses up to 100 mg/kg (2.5 times the RHD on a mg/m2 basis).

Pregnancy: Pregnancy Category C.

Topiramate has demonstrated selective developmental toxicity, including teratogenicity, in experimental animal studies. When oral doses of 20, 100, or 500 mg/kg were administered to pregnant mice during the period of organogenesis, the incidence of fetal malformations (primarily craniofacial defects) was increased at all doses. The low dose is approximately 0.2 times the recommended human dose (RHD=400 mg/day) on a mg/m2 basis. Fetal body weights and skeletal ossification were reduced at 500 mg/kg in conjunction with decreased maternal body weight gain.

In rat studies (oral doses of 20, 100, and 500 mg/kg or 0.2, 2.5, 30, and 400 mg/kg), the frequency of limb malformations (ectrodactyly, micromelia, and amelia) was increased among the offspring of dams treated with 400 mg/kg (10 times the RHD on a mg/m2 basis) or greater during the organogenesis period of pregnancy. Embryotoxicity (reduced fetal body weights, increased incidence of structural variations) was observed at doses as low as 20 mg/kg (0.5 times the RHD on a mg/m2 basis). Clinical signs of maternal toxicity were seen at 400 mg/kg and above, and maternal body weight gain was reduced during treatment with 100 mg/kg or greater.

In rabbit studies (20, 60, and 180 mg/kg or 10, 35, and 120 mg/kg orally during organogenesis), embryo/fetal mortality was increased at 35 mg/kg (2 times the RHD on a mg/m2 basis) or greater, and teratogenic effects (primarily rib and vertebral malformations) were observed at 120 mg/kg (6 times the RHD on a mg/m2 basis). Evidence of maternal toxicity (decreased body weight gain, clinical signs, and/or mortality) was seen at 35 mg/kg and above.

When female rats were treated during the latter part of gestation and throughout lactation (0.2, 4, 20, and 100 mg/kg or 2, 20, and 200 mg/kg), offspring exhibited decreased viability and delayed physical development at 200 mg/kg (5 times the RHD on a mg/m2 basis) and reductions in pre- and/or postweaning body weight gain at 2 mg/kg (0.05 times the RHD on a mg/m2 basis) and above. Maternal toxicity (decreased body weight gain, clinical signs) was evident at 100 mg/kg or greater.

In a rat embryo/fetal development study with a postnatal component (0.2, 2.5, 30, or 400 mg/kg during organogenesis; noted above), pups exhibited delayed physical development at 400 mg/kg (10 times the RHD on a mg/m2 basis) and persistent reductions in body weight gain at 30 mg/kg (1 times the RHD on a mg/m2 basis) and higher.

There are no studies using topiramate in pregnant women. Topiramate should be used during pregnancy only if the potential benefit outweighs the potential risk to the fetus.

In post-marketing experience, cases of hypospadias have been reported in male infants exposed in utero to topiramate, with or without other anticonvulsants; however, a causal relationship with topiramate has not been established.

To provide information regarding the effects of in utero exposure to topiramate tablets, physicians are advised to recommend that pregnant patients taking topiramate tablets enroll in the NAAED Pregnancy Registry. This can be done by calling the toll free number, 1-888-233-2334, and must be done by patients themselves. Information on the registry can also be found at the website http://www.aedpregnancyregistry.org/.

Labor and Delivery:

In studies of rats where dams were allowed to deliver pups naturally, no drug-related effects on gestation length or parturition were observed at dosage levels up to 200 mg/kg/day.

The effect of topiramate on labor and delivery in humans is unknown.

Nursing Mothers:

Topiramate is excreted in the milk of lactating rats. The excretion of topiramate in human milk has not been evaluated in controlled studies. Limited observations in patients suggest an extensive secretion of topiramate into breast milk. Since many drugs are excreted in human milk, and because the potential for serious adverse reactions in nursing infants to topiramate is unknown, the potential benefit to the mother should be weighed against the potential risk to the infant when considering recommendations regarding nursing.

Pediatric Use:

Safety and effectiveness in patients below the age of 2 years have not been established for the adjunctive therapy treatment of partial onset seizures, primary generalized tonic-clonic seizures, or seizures associated with Lennox-Gastaut syndrome. Safety and effectiveness in patients below the age of 10 years have not been established for the monotherapy treatment of epilepsy. Topiramate is associated with metabolic acidosis. Chronic untreated metabolic acidosis in pediatric patients may cause osteomalacia/rickets and may reduce growth rates. A reduction in growth rate may eventually decrease the maximal height achieved. The effect of topiramate on growth and bone-related sequelae has not been systematically investigated (see WARNINGS).

Geriatric Use:

In clinical trials, 3% of patients were over 60. No age related difference in effectiveness or adverse effects were evident. However, clinical studies of topiramate did not include sufficient numbers of subjects aged 65 and over to determine whether they respond differently than younger subjects. Dosage adjustment may be necessary for elderly with impaired renal function (creatinine clearance rate ≤70 mL/min/1.73 m2) due to reduced clearance of topiramate (see CLINICAL PHARMACOLOGY and DOSAGE AND ADMINISTRATION).

Race and Gender Effects:

Evaluation of effectiveness and safety in clinical trials has shown no race or gender related effects.

ADVERSE REACTIONS SECTION

The data described in the following section were obtained using topiramate tablets.

Monotherapy Epilepsy

The adverse events in the controlled trial that occurred most commonly in adults in the 400 mg/day group and at a rate higher than the 50 mg/day group were: paresthesia, weight decrease, somnolence, anorexia, dizziness, and difficulty with memory NOS [see Table 5].

The adverse events in the controlled trial that occurred most commonly in children (10 years up to 16 years of age) in the 400 mg/day group and at a rate higher than the 50 mg/day group were: weight decrease, upper respiratory tract infection, paresthesia, anorexia, diarrhea, and mood problems [see Table 6].

Approximately 21% of the 159 adult patients in the 400 mg/day group who received topiramate as monotherapy in the controlled clinical trial discontinued therapy due to adverse events. Adverse events associated with discontinuing therapy (≥2%) included depression, insomnia, difficulty with memory (NOS), somnolence, paresthesia, psychomotor slowing, dizziness, and nausea.

Approximately 12% of the 57 pediatric patients in the 400 mg/day group who received topiramate as monotherapy in the controlled clinical trial discontinued therapy due to adverse events. Adverse events associated with discontinuing therapy (≥5%) included difficulty with concentration/attention.

The prescriber should be aware that these data cannot be used to predict the frequency of adverse events in the course of usual medical practice where patient characteristics and other factors may differ from those prevailing during the clinical study. Similarly, the cited frequencies cannot be directly compared with data obtained from other clinical investigations involving different treatments, uses, or investigators. Inspection of these frequencies, however, does provide the prescribing physician with a basis to estimate the relative contribution of drug and non-drug factors to the adverse event incidences in the population studied.

Table 5: Incidence of Treatment-Emergent Adverse Events in the Monotherapy Epilepsy Trial in Adultsa Where Rate Was at Least 2% in the 400 mg/day Topiramate Group and Greater Than the Rate in the 50 mg/day Topiramate Group
Topiramate Dosage (mg/day)
Body System/
Adverse Event 50
(N= 160) 400
(N=159)

a Values represent the percentage of patients reporting a given adverse event. Patients may have reported more than one adverse event during the study and can be included in more than one adverse event category.

Body as a Whole-General Disorders
Asthenia 4 6
Leg Pain 2 3
Chest Pain 1 2
Central & Peripheral Nervous System Disorders
Paresthesia 21 40
Dizziness 13 14
Hypoaesthesia 4 5
Ataxia 3 4
Hypertonia 0 3
Gastro-Intestinal System Disorders
Diarrhea 5 6
Constipation 1 4
Gastritis 0 3
Dry Mouth 1 3
Gastroesophageal Reflux 1 2
Liver and Biliary System Disorders
Gamma-GT Increased 1 3
Metabolic and Nutritional Disorders
Weight Decrease 6 16
Psychiatric Disorders
Somnolence 9 15
Anorexia 4 14
Difficulty with Memory NOS 5 10
Insomnia 8 9
Depression 7 9
Difficulty with Concentration/Attention 7 8
Anxiety 4 6
Psychomotor Slowing 3 5
Mood Problems 2 5
Confusion 3 4
Cognitive Problem NOS 1 4
Libido Decreased 0 3
Reproductive Disorders, Female
Vaginal Hemorrhage 0 3
Red Blood Cell Disorders
Anemia 1 2
Resistance Mechanism Disorders
Infection Viral 6 8
Infection 2 3
Respiratory System Disorders
Bronchitis 3 4
Rhinitis 2 4
Dyspnea 1 2
Skin and Appendages Disorders
Rash 1 4
Pruritus 1 4
Acne 2 3
Special Senses Other, Disorders
Taste Perversion 3 5
Urinary System Disorders
Cystitis 1 3
Renal Calculus 0 3
Urinary Tract Infection 1 2
Dysuria 0 2
Micturition Frequency 0 2

Table 6: Incidence of Treatment-Emergent Adverse Events in the Monotherapy Epilepsy Trial in Children Ages 10 up to 16 Yearsa Where Rate Was at Least 5% in the 400 mg/day Topiramate Group and Greater Than the Rate in the 50 mg/day Topiramate Group
Topiramate Dosage (mg/day)
Body System/
Adverse Event 50
(N=57) 400
(N=57)

a Values represent the percentage of patients reporting a given adverse event. Patients may have reported more than one adverse event during the study and can be included in more than one adverse event category.

Body as a Whole-General Disorders
Fever 0 9
Central & Peripheral Nervous System Disorders
Paresthesia 2 16
Gastro-Intestinal System Disorders
Diarrhea 5 11
Metabolic and Nutritional Disorders
Weight Decrease 7 21
Psychiatric Disorders
Anorexia 11 14
Mood Problems 2 11
Difficulty with Concentration/Attention 4 9
Cognitive Problems NOS 0 7
Nervousness 4 5
Resistance Mechanism Disorders
Infection Viral 4 9
Infection 2 7
Respiratory System Disorders
Upper Respiratory Tract Infection 16 18
Rhinitis 2 7
Bronchitis 2 7
Sinusitis 2 5
Skin and Appendages Disorders
Alopecia 2 5

Adjunctive Therapy Epilepsy

The most commonly observed adverse events associated with the use of topiramate at dosages of 200 to 400 mg/day in controlled trials in adults with partial onset seizures, primary generalized tonic-clonic seizures, or Lennox-Gastaut syndrome, that were seen at greater frequency in topiramate-treated patients and did not appear to be dose-related were: somnolence, dizziness, ataxia, speech disorders and related speech problems, psychomotor slowing, abnormal vision, difficulty with memory, paresthesia and diplopia [see Table 7]. The most common dose-related adverse events at dosages of 200 to 1,000 mg/day were: fatigue, nervousness, difficulty with concentration or attention, confusion, depression, anorexia, language problems, anxiety, mood problems, and weight decrease [see Table 9].

Adverse events associated with the use of topiramate at dosages of 5 to 9 mg/kg/day in controlled trials in pediatric patients with partial onset seizures, primary generalized tonic-clonic seizures, or Lennox-Gastaut syndrome, that were seen at greater frequency in topiramate-treated patients were: fatigue, somnolence, anorexia, nervousness, difficulty with concentration/attention, difficulty with memory, aggressive reaction, and weight decrease [see Table 10].

In controlled clinical trials in adults, 11% of patients receiving topiramate 200 to 400 mg/day as adjunctive therapy discontinued due to adverse events. This rate appeared to increase at dosages above 400 mg/day. Adverse events associated with discontinuing therapy included somnolence, dizziness, anxiety, difficulty with concentration or attention, fatigue, and paresthesia and increased at dosages above 400 mg/day. None of the pediatric patients who received topiramate adjunctive therapy at 5 to 9 mg/kg/day in controlled clinical trials discontinued due to adverse events.

Approximately 28% of the 1,757 adults with epilepsy who received topiramate at dosages of 200 to 1,600 mg/day in clinical studies discontinued treatment because of adverse events; an individual patient could have reported more than one adverse event. These adverse events were: psychomotor slowing (4%), difficulty with memory (3.2%), fatigue (3.2%), confusion (3.1%), somnolence (3.2%), difficulty with concentration/attention (2.9%), anorexia (2.7%), depression (2.6%), dizziness (2.5%), weight decrease (2.5%), nervousness (2.3%), ataxia (2.1%), and paresthesia (2%). Approximately 11% of the 310 pediatric patients who received topiramate at dosages up to 30 mg/kg/day discontinued due to adverse events. Adverse events associated with discontinuing therapy included aggravated convulsions (2.3%), difficulty with concentration/attention (1.6%), language problems (1.3%), personality disorder (1.3%), and somnolence (1.3%).

Incidence in Epilepsy Controlled Clinical Trials - Adjunctive Therapy – Partial Onset Seizures, Primary Generalized Tonic-Clonic Seizures, and Lennox-Gastaut Syndrome

Table 7 lists treatment-emergent adverse events that occurred in at least 1% of adults treated with 200 to 400 mg/day topiramate in controlled trials that were numerically more common at this dose than in the patients treated with placebo. In general, most patients who experienced adverse events during the first eight weeks of these trials no longer experienced them by their last visit. Table 10 lists treatment-emergent adverse events that occurred in at least 1% of pediatric patients treated with 5 to 9 mg/kg topiramate in controlled trials that were numerically more common than in patients treated with placebo.

The prescriber should be aware that these data were obtained when topiramate was added to concurrent antiepileptic drug therapy and cannot be used to predict the frequency of adverse events in the course of usual medical practice where patient characteristics and other factors may differ from those prevailing during clinical studies. Similarly, the cited frequencies cannot be directly compared with data obtained from other clinical investigations involving different treatments, uses, or investigators. Inspection of these frequencies, however, does provide the prescribing physician with a basis to estimate the relative contribution of drug and non-drug factors to the adverse event incidences in the population studied.

Other Adverse Events Observed During Double-Blind Epilepsy Adjunctive Therapy Trials

Other events that occurred in more than 1% of adults treated with 200 to 400 mg of topiramate in placebo-controlled epilepsy trials but with equal or greater frequency in the placebo group were: headache, injury, anxiety, rash, pain, convulsions aggravated, coughing, fever, diarrhea, vomiting, muscle weakness, insomnia, personality disorder, dysmenorrhea, upper respiratory tract infection, and eye pain.

Table 7: Incidence of Treatment-Emergent Adverse Events in Placebo-Controlled, Add-On Epilepsy Trials in Adultsa,b Where Rate Was > 1% in Any Topiramate Group and Greater Than the Rate in Placebo-Treated Patients
Topiramate Dosage (mg/day)
Body System/
Adverse Eventc Placebo
(N=291) 200 to 400
(N=183) 600 to 1,000
(N=414)

a Patients in these add-on trials were receiving 1 to 2 concomitant antiepileptic drugs in addition to topiramate or placebo.

b Values represent the percentage of patients reporting a given adverse event. Patients may have reported more than one adverse event during the study and can be included in more than one adverse event category.

c Adverse events reported by at least 1% of patients in the topiramate 200 to 400 mg/day group and more common than in the placebo group are listed in this table.

Body as a Whole-General Disorders
Fatigue 13 15 30
Asthenia 1 6 3
Back Pain 4 5 3
Chest Pain 3 4 2
Influenza-Like Symptoms 2 3 4
Leg Pain 2 2 4
Hot Flushes 1 2 1
Allergy 1 2 3
Edema 1 2 1
Body Odor 0 1 0
Rigors 0 1 <1
Central & Peripheral Nervous System Disorders
Dizziness 15 25 32
Ataxia 7 16 14
Speech Disorders/Related Speech Problems 2 13 11
Paresthesia 4 11 19
Nystagmus 7 10 11
Tremor 6 9 9
Language Problems 1 6 10
Coordination Abnormal 2 4 4
Hypoaesthesia 1 2 1
Gait Abnormal 1 3 2
Muscle Contractions Involuntary 1 2 2
Stupor 0 2 1
Vertigo 1 1 2
Gastro-Intestinal System Disorders
Nausea 8 10 12
Dyspepsia 6 7 6
Abdominal Pain 4 6 7
Constipation 2 4 3
Gastroenteritis 1 2 1
Dry Mouth 1 2 4
Gingivitis <1 1 1
GI Disorder <1 1 0
Hearing and Vestibular Disorders
Hearing Decreased 1 2 1
Metabolic and Nutritional Disorders
Weight Decrease 3 9 13
Muscle-Skeletal System Disorders
Myalgia 1 2 2
Skeletal Pain 0 1 0
Platelet, Bleeding, & Clotting Disorders
Epistaxis 1 2 1
Psychiatric Disorders
Somnolence 12 29 28
Nervousness 6 16 19
Psychomotor Slowing 2 13 21
Difficulty with Memory 3 12 14
Anorexia 4 10 12
Confusion 5 11 14
Depression 5 5 13
Difficulty with Concentration/Attention 2 6 14
Mood Problems 2 4 9
Agitation 2 3 3
Aggressive Reaction 2 3 3
Emotional Lability 1 3 3
Cognitive Problems 1 3 3
Libido Decreased 1 2 <1
Apathy 1 1 3
Depersonalization 1 1 2
Reproductive Disorders, Female
Breast Pain 2 4 0
Amenorrhea 1 2 2
Menorrhagia 0 2 1
Menstrual Disorder 1 2 1
Reproductive Disorders, Male
Prostatic Disorder <1 2 0
Resistance Mechanism Disorders
Infection 1 2 1
Infection Viral 1 2 <1
Moniliasis <1 1 0
Respiratory System Disorders
Pharyngitis 2 6 3
Rhinitis 6 7 6
Sinusitis 4 5 6
Dyspnea 1 1 2
Skin and Appendages Disorders
Skin Disorder <1 2 1
Sweating Increased <1 1 <1
Rash Erythematous <1 1 <1
Special Sense Other, Disorders
Taste Perversion 0 2 4
Urinary System Disorders
Hematuria 1 2 <1
Urinary Tract Infection 1 2 3
Micturition Frequency 1 1 2
Urinary Incontinence <1 2 1
Urine Abnormal 0 1 <1
Vision Disorders
Vision Abnormal 2 13 10
Diplopia 5 10 10
White Cell and RES Disorders
Leukopenia 1 2 1

Incidence in Study 119 – Add-On Therapy– Adults with Partial Onset Seizures

Study 119 was a randomized, double-blind, placebo-controlled, parallel group study with 3 treatment arms: 1) placebo; 2) topiramate 200 mg/day with a 25 mg/day starting dose, increased by 25 mg/day each week for 8 weeks until the 200 mg/day maintenance dose was reached; and 3) topiramate 200 mg/day with a 50 mg/day starting dose, increased by 50 mg/day each week for 4 weeks until the 200 mg/day maintenance dose was reached. All patients were maintained on concomitant carbamazepine with or without another concomitant antiepileptic drug.

The incidence of adverse events (Table 8) did not differ significantly between the 2 topiramate regimens. Because the frequencies of adverse events reported in this study were markedly lower than those reported in the previous epilepsy studies, they cannot be directly compared with data obtained in other studies.

Table 8: Incidence of Treatment-Emergent Adverse Events in Study 119a,b Where Rate Was ≥ 2% in the Topiramate Group and Greater Than the Rate in Placebo-Treated Patients
Topiramate Dosage (mg/day)
Body System/
Adverse Eventc Placebo
(N=92) 200
(N=171)

a Patients in these add-on trials were receiving 1 to 2 concomitant antiepileptic drugs in addition to topiramate or placebo.

b Values represent the percentage of patients reporting a given adverse event. Patients may have reported more than one adverse event during the study and can be included in more than one adverse event category.

c Adverse events reported by at least 2% of patients in the topiramate 200 mg/day group and more common than in the placebo group are listed in this table.

Body as a Whole-General Disorders
Fatigue 4 9
Chest Pain 1 2
Cardiovascular Disorders, General
Hypertension 0 2
Central & Peripheral Nervous System Disorders
Paresthesia 2 9
Dizziness 4 7
Tremor 2 3
Hypoasthesia 0 2
Leg Cramps 0 2
Language Problems 0 2
Gastro-Intestinal System Disorders
Abdominal Pain 3 5
Constipation 0 4
Diarrhea 1 2
Dyspepsia 0 2
Dry Mouth 0 2
Hearing and Vestibular Disorders
Tinnitus 0 2
Metabolic and Nutritional Disorders
Weight Decrease 4 8
Psychiatric Disorders
Somnolence 9 15
Anorexia 7 9
Nervousness 2 9
Difficulty with Concentration/Attention 0 5
Insomnia 3 4
Difficulty with Memory 1 2
Aggressive Reaction 0 2
Respiratory System Disorders
Rhinitis 0 4
Urinary System Disorders
Cystitis 0 2
Vision Disorders
Diplopia 0 2
Vision Abnormal 0 2

Table 9: Incidence (%) of Dose-Related Adverse Events From Placebo-Controlled, Add-On Trials in Adults with Partial Onset Seizuresa
Topiramate Dosage (mg/day)
Adverse Event Placebo
(N = 216) 200
(N = 45) 400
(N = 68) 600 to 1,000
(N = 414)

a Dose-response studies were not conducted for other adult indications or for pediatric indications.

Fatigue 13 11 12 30
Nervousness 7 13 18 19
Difficulty with Concentration/Attention 1 7 9 14
Confusion 4 9 10 14
Depression 6 9 7 13
Anorexia 4 4 6 12
Language problems <1 2 9 10
Anxiety 6 2 3 10
Mood problems 2 0 6 9
Weight decrease 3 4 9 13

Table 10: Incidence (%) of Treatment-Emergent Adverse Events in Placebo-Controlled, Add-On Epilepsy Trials in Pediatric Patients Ages 2 to 16 Yearsa,b (Events that Occurred in at Least 1% of Topiramate-Treated Patients and Occurred More Frequently in Topiramate-Treated Than Placebo-Treated Patients)
Body System/
Adverse Event Placebo
(N=101) Topiramate
(N=98)

a Patients in these add-on trials were receiving 1 to 2 concomitant antiepileptic drugs in addition to topiramate or placebo.

b Values represent the percentage of patients reporting a given adverse event. Patients may have reported more than one adverse event during the study and can be included in more than one adverse event category.

Body as a Whole - General Disorders
Fatigue 5 16
Injury 13 14
Allergic Reaction 1 2
Back Pain 0 1
Pallor 0 1
Cardiovascular Disorders, General
Hypertension 0 1
Central & Peripheral Nervous System Disorders
Gait Abnormal 5 8
Ataxia 2 6
Hyperkinesia 4 5
Dizziness 2 4
Speech Disorders/Related Speech Problems 2 4
Hyporeflexia 0 2
Convulsions Grand Mal 0 1
Fecal Incontinence 0 1
Paresthesia 0 1
Gastro-Intestinal System Disorders
Nausea 5 6
Saliva Increased 4 6
Constipation 4 5
Gastroenteritis 2 3
Dysphagia 0 1
Flatulence 0 1
Gastroesophageal Reflux 0 1
Glossitis 0 1
Gum Hyperplasia 0 1
Heart Rate and Rhythm Disorders
Bradycardia 0 1
Metabolic and Nutritional Disorders
Weight Decrease 1 9
Thirst 1 2
Hypoglycemia 0 1
Weight Increase 0 1
Platelet, Bleeding, & Clotting Disorders
Purpura 4 8
Epistaxis 1 4
Hematoma 0 1
Prothrombin Increased 0 1
Thrombocytopenia 0 1
Psychiatric Disorders
Somnolence 16 26
Anorexia 15 24
Nervousness 7 14
Personality Disorder (Behavior Problems) 9 11
Difficulty with Concentration/Attention 2 10
Aggressive Reaction 4 9
Insomnia 7 8
Difficulty with Memory NOS 0 5
Confusion 3 4
Psychomotor Slowing 2 3
Appetite Increased 0 1
Neurosis 0 1
Reproductive Disorders, Female
Leukorrhoea 0 2
Resistance Mechanism Disorders
Infection Viral 3 7
Respiratory System Disorders
Pneumonia 1 5
Respiratory Disorder 0 1
Skin and Appendages Disorders
Skin Disorder 2 3
Alopecia 1 2
Dermatitis 0 2
Hypertrichosis 1 2
Rash Erythematous 0 2
Eczema 0 1
Seborrhoea 0 1
Skin Discoloration 0 1
Urinary System Disorders
Urinary Incontinence 2 4
Nocturia 0 1
Vision Disorders
Eye Abnormality 1 2
Vision Abnormal 1 2
Diplopia 0 1
Lacrimation Abnormal 0 1
Myopia 0 1
White Cell and RES Disorders
Leukopenia 0 2

Other Adverse Events Observed During All Epilepsy Clinical Trials

Topiramate has been administered to 2,246 adults and 427 pediatric patients with epilepsy during all clinical studies, only some of which were placebo controlled. During these studies, all adverse events were recorded by the clinical investigators using terminology of their own choosing. To provide a meaningful estimate of the proportion of individuals having adverse events, similar types of events were grouped into a smaller number of standardized categories using modified WHOART dictionary terminology. The frequencies presented represent the proportion of patients who experienced an event of the type cited on at least one occasion while receiving topiramate. Reported events are included except those already listed in the previous tables or text, those too general to be informative, and those not reasonably associated with the use of the drug.

Events are classified within body system categories and enumerated in order of decreasing frequency using the following definitions: frequent occurring in at least 1/100 patients; infrequent occurring in 1/100 to 1/1000 patients; rare occurring in fewer than 1/1000 patients.

Autonomic Nervous System Disorders: Infrequent: vasodilation.

Body as a Whole: Frequent: syncope. Infrequent: abdomen enlarged. Rare: alcohol intolerance.

Cardiovascular Disorders, General: Infrequent: hypotension, postural hypotension, angina pectoris.

Central & Peripheral Nervous System Disorders: Infrequent : neuropathy, apraxia, hyperaesthesia, dyskinesia, dysphonia, scotoma, ptosis, dystonia, visual field defect, encephalopathy, EEG abnormal. Rare: upper motor neuron lesion, cerebellar syndrome, tongue paralysis.

Gastrointestinal System Disorders: Infrequent: hemorrhoids, stomatitis, melena, gastritis, esophagitis. Rare: tongue edema.

Heart Rate and Rhythm Disorders: Infrequent: AV block.

Liver and Biliary System Disorders: Infrequent: SGPT increased, SGOT increased.

Metabolic and Nutritional Disorders: Infrequent: dehydration, hypokalemia, alkaline phosphatase increased, hypocalcemia, hyperlipemia, hyperglycemia, xerophthalmia, diabetes mellitus. Rare: hyperchloremia, hypernatremia, hyponatremia, hypocholesterolemia, hypophosphatemia, creatinine increased.

Musculoskeletal System Disorders: Frequent: arthralgia. Infrequent: arthrosis.

Neoplasms: Infrequent: thrombocythemia. Rare: polycythemia.

Platelet, Bleeding, and Clotting Disorders: Infrequent: gingival bleeding, pulmonary embolism.

Psychiatric Disorders: Frequent: impotence, hallucination, psychosis, suicide attempt. Infrequent: euphoria, paranoid reaction, delusion, paranoia, delirium, abnormal dreaming. Rare: libido increased, manic reaction.

Red Blood Cell Disorders: Frequent: anemia. Rare: marrow depression, pancytopenia.

Reproductive Disorders, Male: Infrequent: ejaculation disorder, breast discharge.

Skin and Appendages Disorders: Infrequent: urticaria, photosensitivity reaction, abnormal hair texture. Rare: chloasma.

Special Senses Other, Disorders: Infrequent: taste loss, parosmia.

Urinary System Disorders: Infrequent: urinary retention, face edema, renal pain, albuminuria, polyuria, oliguria.

Vascular (Extracardiac) Disorders: Infrequent: flushing, deep vein thrombosis, phlebitis. Rare: vasospasm.

Vision Disorders: Frequent: conjunctivitis. Infrequent: abnormal accommodation, photophobia, strabismus. Rare: mydriasis, iritis.

White Cell and Reticuloendothelial System Disorders: Infrequent: lymphadenopathy, eosinophilia, lymphopenia, granulocytopenia. Rare: lymphocytosis.

Postmarketing and Other Experience

In addition to the adverse experiences reported during clinical testing of topiramate, the following adverse experiences have been reported worldwide in patients receiving topiramate post-approval.

These adverse experiences have not been listed above and data are insufficient to support an estimate of their incidence or to establish causation. The listing is alphabetized: bullous skin reactions (including erythema multiforme, Stevens-Johnson syndrome, toxic epidermal necrolysis), hepatic failure (including fatalities), hepatitis, maculopathy, pancreatitis, pemphigus, and renal tubular acidosis.

DRUG ABUSE AND DEPENDENCE

The abuse and dependence potential of topiramate has not been evaluated in human studies

OVERDOSAGE SECTION

Overdoses of topiramate have been reported. Signs and symptoms included convulsions, drowsiness, speech disturbance, blurred vision, diplopia, mentation impaired, lethargy, abnormal coordination, stupor, hypotension, abdominal pain, agitation, dizziness and depression. The clinical consequences were not severe in most cases, but deaths have been reported after poly-drug overdoses involving topiramate.

Topiramate overdose has resulted in severe metabolic acidosis (see WARNINGS).

A patient who ingested a dose between 96 and 110 g topiramate was admitted to hospital with coma lasting 20 to 24 hours followed by full recovery after 3 to 4 days.

In acute topiramate overdose, if the ingestion is recent, the stomach should be emptied immediately by lavage or by induction of emesis. Activated charcoal has been shown to adsorb topiramate in vitro. Treatment should be appropriately supportive. Hemodialysis is an effective means of removing topiramate from the body.

DOSAGE & ADMINISTRATION

Epilepsy

In the controlled add-on trials, no correlation has been demonstrated between trough plasma concentrations of topiramate and clinical efficacy. No evidence of tolerance has been demonstrated in humans. Doses above 400 mg/day (600, 800, or 1000 mg/day) have not been shown to improve responses in dose-response studies in adults with partial onset seizures.

It is not necessary to monitor topiramate plasma concentrations to optimize topiramate therapy. On occasion, the addition of topiramate to phenytoin may require an adjustment of the dose of phenytoin to achieve optimal clinical outcome. Addition or withdrawal of phenytoin and/or carbamazepine during adjunctive therapy with topiramate may require adjustment of the dose of topiramate. Because of the bitter taste, tablets should not be broken.

Topiramate tablets can be taken without regard to meals.

Monotherapy Use

The recommended dose for topiramate monotherapy in adults and children 10 years of age and older is 400 mg/day in two divided doses. Approximately 58% of patients randomized to 400 mg/day achieved this maximal dose in the monotherapy controlled trial; the mean dose achieved in the trial was 275 mg/day. The dose should be achieved by titrating according to the following schedule:

 | Morning Dose | Evening Dose
Week 1 | 25 mg | 25 mg
Week 2 | 50 mg | 50 mg
Week 3 | 75 mg | 75 mg
Week 4 | 100 mg | 100 mg
Week 5 | 150 mg | 150 mg
Week 6 | 200 mg | 200 mg

Adjunctive Therapy UseAdults (17 Years of Age and Over) - Partial Seizures, Primary Generalized Tonic-Clonic Seizures, or Lennox-Gastaut Syndrome

The recommended total daily dose of topiramate as adjunctive therapy in adults with partial seizures is 200 to 400 mg/day in two divided doses, and 400 mg/day in two divided doses as adjunctive treatment in adults with primary generalized tonic-clonic seizures. It is recommended that therapy be initiated at 25 to 50 mg/day followed by titration to an effective dose in increments of 25 to 50 mg/week. Titrating in increments of 25 mg/week may delay the time to reach an effective dose. Daily doses above 1,600 mg have not been studied.

In the study of primary generalized tonic-clonic seizures the initial titration rate was slower than in previous studies; the assigned dose was reached at the end of 8 weeks (see CLINICAL STUDIES, Adjunctive Therapy Controlled Trials in Patients With Primary Generalized Tonic-Clonic Seizures).

Pediatric Patients (Ages 2 to 16 Years)– Partial Seizures, Primary Generalized Tonic-Clonic Seizures, or Lennox-Gastaut Syndrome

The recommended total daily dose of topiramate as adjunctive therapy for patients with partial seizures, primary generalized tonic-clonic seizures, or seizures associated with Lennox-Gastaut syndrome is approximately 5 to 9 mg/kg/day in two divided doses. Titration should begin at 25 mg (or less, based on a range of 1 to 3 mg/kg/day) nightly for the first week. The dosage should then be increased at 1- or 2-week intervals by increments of 1 to 3 mg/kg/day (administered in two divided doses), to achieve optimal clinical response. Dose titration should be guided by clinical outcome.

In the study of primary generalized tonic-clonic seizures the initial titration rate was slower than in previous studies; the assigned dose of 6 mg/kg/day was reached at the end of 8 weeks (see CLINICAL STUDIES, Adjunctive Therapy Controlled Trials in Patients With Primary Generalized Tonic-Clonic Seizures).

Patients with Renal Impairment:

In renally impaired subjects (creatinine clearance less than 70 mL/min/1.73 m2), one half of the usual adult dose is recommended. Such patients will require a longer time to reach steady-state at each dose.

Geriatric Patients (Ages 65 Years and Over):

Dosage adjustment may be indicated in the elderly patient when impaired renal function (creatinine clearance rate ≤70 mL/min/1.73 m2) is evident (see DOSAGE AND ADMINISTRATION: Patients with Renal Impairment and CLINICAL PHARMACOLOGY: Special Populations: Age, Gender, and Race).

Patients Undergoing Hemodialysis:

Topiramate is cleared by hemodialysis at a rate that is 4 to 6 times greater than a normal individual. Accordingly, a prolonged period of dialysis may cause topiramate concentration to fall below that required to maintain an anti-seizure effect. To avoid rapid drops in topiramate plasma concentration during hemodialysis, a supplemental dose of topiramate may be required. The actual adjustment should take into account 1) the duration of dialysis period, 2) the clearance rate of the dialysis system being used, and 3) the effective renal clearance of topiramate in the patient being dialyzed.

Patients with Hepatic Disease:

In hepatically impaired patients topiramate plasma concentrations may be increased. The mechanism is not well understood.

HOW SUPPLIED SECTION

Topiramate tablets are available as debossed, film-coated, circular tablets in the following strengths and colors:

25 mg white (coded "S" on one side; "707" on the other)

50 mg yellow (coded "S" on one side; "710" on the other)

100 mg yellow (coded "S" on one side; "711" on the other)

200 mg brown (coded "S" on one side; "712" on the other)

They are supplied as follows:

25 mg tablets Bottles of 30's with Child Resistant Cap… …………NDC 62756-707-83

Bottles of 60's with Child Resistant Cap… …………NDC 62756-707-86

Bottles of 100's with Child Resistant Cap… … … …NDC 62756-707-88

Bottles of 100's with Non Child Resistant Cap………NDC 62756-707-08

Bottles of 500's with Non Child Resistant Cap………NDC 62756-707-13

Bottles of 1000's with Non Child Resistant Cap… …NDC 62756-707-18

50 mg tablets Bottles of 30's with Child Resistant Cap… …………NDC 62756-710-83

Bottles of 60's with Child Resistant Cap… …………NDC 62756-710-86

Bottles of 100's with Child Resistant Cap… … … …NDC 62756-710-88

Bottles of 100's with Non Child Resistant Cap………NDC 62756-710-08

Bottles of 500's with Non Child Resistant Cap………NDC 62756-710-13

Bottles of 1000's with Non Child Resistant Cap… …NDC 62756-710-18

100 mg tablets Bottles of 30's with Child Resistant Cap… …………NDC 62756-711-83

Bottles of 60's with Child Resistant Cap… …………NDC 62756-711-86

Bottles of 100's with Child Resistant Cap… … … …NDC 62756-711-88

Bottles of 100's with Non Child Resistant Cap………NDC 62756-711-08

Bottles of 500's with Non Child Resistant Cap………NDC 62756-711-13

Bottles of 1000's with Non Child Resistant Cap… …NDC 62756-711-18

200 mg tablets Bottles of 30's with Child Resistant Cap… …………NDC 62756-712-83

Bottles of 60's with Child Resistant Cap… …………NDC 62756-712-86

Bottles of 100's with Child Resistant Cap… … … …NDC 62756-712-88

Bottles of 100's with Non Child Resistant Cap………NDC 62756-712-08

Bottles of 500's with Non Child Resistant Cap………NDC 62756-712-13

Bottles of 1000's with Non Child Resistant Cap… …NDC 62756-712-18

Store at 20° to 25°C (68° to 77°F); excursions permitted to 15° to 30°C (59° to 86°F) [See USP Controlled Room Temperature]. Protect from moisture. Dispense in a tight container

PATIENT MEDICATION INFORMATION

Topiramate Tablets

Read this Medication Guide before you start taking topiramate tablets and each time you get a refill. There may be new information. This information does not take the place of talking to your healthcare provider about your medical condition or treatment. If you have any questions about topiramate tablets, talk to your healthcare provider or pharmacist.

What is the most important information I should know about topiramate tablets?

- Topiramate tablets may cause eye problems. Serious eye problems include:
-
  - any sudden decrease in vision with or without eye pain and redness
  - a blockage of fluid in the eye causing increased pressure in the eye (secondary angle closure glaucoma).
  - These eye problems can lead to permanent loss of vision if not treated. You should call your healthcare provider right away if you have any new eye symptoms.
- Topiramate tablets may cause decreased sweating and increased body temperature (fever). People, especially children, should be watched for signs of decreased sweating and fever, especially in hot temperatures. Some people may need to be hospitalized for this condition.
- Like other antiepileptic drugs, topiramate tablets may cause suicidal thoughts or actions in a very small number of people, about 1 in 500.

Call a healthcare provider right away if you have any of these symptoms, especially if they are new, worse, or worry you:

- thoughts about suicide or dying
- attempts to commit suicide
- new or worse depression
- new or worse anxiety
- feeling agitated or restless
- panic attacks
- trouble sleeping (insomnia)
- new or worse irritability
- acting aggressive, being angry, or violent
- acting on dangerous impulses
- an extreme increase in activity and talking (mania)
- other unusual changes in behavior or mood

Do not stop topiramate tablets without first talking to a healthcare provider.

- Stopping topiramate tablets suddenly can cause serious problems.
- Suicidal thoughts or actions can be caused by things other than medicines. If you have suicidal thoughts or actions, your healthcare provider may check for other causes.

How can I watch for early symptoms of suicidal thoughts and actions?

- Pay attention to any changes, especially sudden changes, in mood, behaviors, thoughts, or feelings.
- Keep all follow-up visits with your healthcare provider as scheduled.
- Call your healthcare provider between visits as needed, especially if you are worried about symptoms.

What is topiramate tablet?

Topiramate tablet is a prescription medicine used:

- to treat certain types of seizures (partial onset seizures and primary generalized tonic-clonic seizures) in people 10 years and older
- with other medicines to treat certain types of seizures (partial onset seizures, primary generalized tonic-clonic seizures, and seizures associated with Lennox-Gastaut syndrome) in adults and children 2 years and older

What should I tell my healthcare provider before taking topiramate tablets?

Before taking topiramate tablets, tell your healthcare provider about all your medical conditions, including if you:

- have or have had depression, mood problems or suicidal thoughts or behavior
- have kidney problems, kidney stones, or are getting kidney dialysis
- have a history of metabolic acidosis (too much acid in the blood)
- have liver problems
- have osteoporosis, soft bones, or decreased bone density
- have lung or breathing problems
- have eye problems, especially glaucoma
- have diarrhea
- have a growth problem
- are on a diet high in fat and low in carbohydrates, which is called a ketogenic diet
- are having surgery
- are pregnant or plan to become pregnant. It is not known if topiramate tablets will harm your unborn baby. If you become pregnant while taking topiramate tablets, talk to your healthcare provider about registering with the North American Antiepileptic Drug Pregnancy Registry. You can enroll in this registry by calling 1-888-233-2334. The purpose of this registry is to collect information about the safety of antiepileptic medicine during pregnancy.
- are breastfeeding. It is not known if topiramate passes into breast milk and if it can harm your baby. Talk to your healthcare provider about the best way to feed your baby if you take topiramate tablets.

Tell your healthcare provider about all the medicines you take, including prescription and non-prescription medicines, vitamins, and herbal supplements. Topiramate tablets and other medicines may affect each other causing side effects.

Especially, tell your healthcare provider if you take:

- Valproic acid
- any medicines that impair or decrease your thinking, concentration, or muscle coordination.
- birth control pills. Topiramate tablets may make your birth control pills less effective. Tell your healthcare provider if your menstrual bleeding changes while you are taking birth control pills and topiramate tablets.

Ask you healthcare provider if you are not sure if your medicine is listed above.

Know the medicines you take. Keep a list of them to show your healthcare provider and pharmacist each time you get a new medicine. Do not start a new medicine without talking with your healthcare provider.

How should I take topiramate tablets?

- Take topiramate tablets exactly as prescribed.
- Your healthcare provider may change your dose. Do not change your dose without talking to your healthcare provider.
- Topiramate tablets should be swallowed whole. Do not chew the tablets. They may leave a bitter taste.
- Do not store any medicine and food mixture for later use.
- Topiramate tablets can be taken before, during, or after a meal. Drink plenty of fluids during the day. This may help prevent kidney stones while taking topiramate tablets.
- If you take too many topiramate tablets, call your healthcare provider or poison control center right away or go to the nearest emergency room.
- If you miss a single dose of topiramate tablets, take it as soon as you can. However, if you are within 6 hours of taking your next scheduled dose, wait until then to take your usual dose of topiramate tablets, and skip the missed dose. Do not double your dose. If you have missed more than one dose, you should call your healthcare professional for advice.
- Do not stop taking topiramate tablets without talking to your healthcare provider. Stopping topiramate tablets suddenly may cause serious problems. If you have epilepsy and you stop taking topiramate tablets suddenly, you may have seizures that do not stop. Your healthcare provider will tell you how to stop taking topiramate tablets slowly.
- Your healthcare provider may do blood tests while you take topiramate tablets.

What should I avoid while taking topiramate tablets?

- Do not drink alcohol while taking topiramate tablets. Topiramate tablets and alcohol can affect each other causing side effects such as sleepiness and dizziness.
- Do not drive a car or operate heavy machinery until you know how topiramate tablets affect you. Topiramate tablets can slow your thinking and motor skills.

What are the possible side effects of topiramate tablets?

Topiramate tablets may cause serious side effects including:

See “What is the most important information I should know about topiramate tablets?”

- Metabolic Acidosis. Metabolic acidosis can cause:
-
  - tiredness
  - loss of appetite
  - irregular heartbeat
  - impaired consciousness
- High blood ammonia levels. High ammonia in the blood can affect your mental activities, slow your alertness, make you feel tired, or cause vomiting. This has happened when topiramate tablets are taken with a medicine called valproic acid.
- Kidney stones. Drink plenty of fluids when taking topiramate tablets to decrease your chances of getting kidney stones.
- Effects on Thinking and Alertness. Topiramate tablets may affect how you think, and cause confusion, problems with concentration, attention, memory, or speech. Topiramate tablets may cause depression or mood problems, tiredness, and sleepiness.
- Dizziness or Loss of Muscle Coordination.

Call your healthcare provider right away if you have any of the symptoms above.

The most common side effects of topiramate tablets include:

- tingling of the arms and legs (paresthesia)
- not feeling hungry
- nausea
- a change in the way foods taste
- diarrhea
- weight loss
- nervousness
- upper respiratory tract infection

Tell your healthcare provider about any side effect that bothers you or that does not go away.

These are not all the possible side effects of topiramate tablets. For more information, ask your healthcare provider or pharmacist.

Call your doctor for medical advice about side effects. You may report side effects to FDA at 1-800-FDA-1088.

How should I store topiramate tablets?

- Store topiramate tablets at 20° to 25°C (68° to 77°F); excursions permitted to 15° to 30°C (59° to 86°F).
- Keep topiramate tablets in a tightly closed container
- Keep topiramate tablets dry and away from moisture
- Keep topiramate tablets and all medicines out of the reach of children.

General information about topiramate tablets.

Medicines are sometimes prescribed for purposes other than those listed in a Medication Guide. Do not use topiramate tablet for a condition for which it was not prescribed. Do not give topiramate tablets to other people, even if they have the same symptoms that you have. It may harm them.

This Medication Guide summarizes the most important information about topiramate tablets. If you would like more information, talk with your healthcare provider. You can ask your pharmacist or healthcare provider for information about topiramate tablets that is written for health professionals.

For more information, call 1-800-818-4555

What are the ingredients in topiramate tablets?

Active ingredient: topiramate

Inactive ingredients: anhydrous lactose, microcrystalline cellulose, pregelatinized starch, sodium starch glycolate, magnesium stearate, purified water, polyvinyl alcohol, titanium dioxide, polyethylene glycol and talc.

In addition, individual tablets contain:

50 mg tablets: iron oxide yellow

100 mg tablets: iron oxide yellow, and D&C Yellow # 10 Aluminum Lake

200 mg tablets: iron oxide red, lecithin (soya), and iron oxide black

This Medication Guide has been approved by the U.S. Food and Drug Administration.

Distributed by:

Caraco Pharmaceutical Laboratories, Ltd.

1150 Elijah McCoy Drive, Detroit, MI 48202

Manufactured by:

Sun Pharmaceutical Industries Ltd.

Acme Plaza, Andheri-Kurla Road,

Andheri (East), Mumbai - 400 059, India.

ISS. 07/2009

PGPI0101A

PACKAGE LABEL.PRINCIPAL DISPLAY PANEL - Label - 25 mg

NDC 62756-707-83

Topiramate Tablets

25 mg

Rx only

30 TABLETS

SUN PHARMACEUTICAL INDUSTRIES LTD.